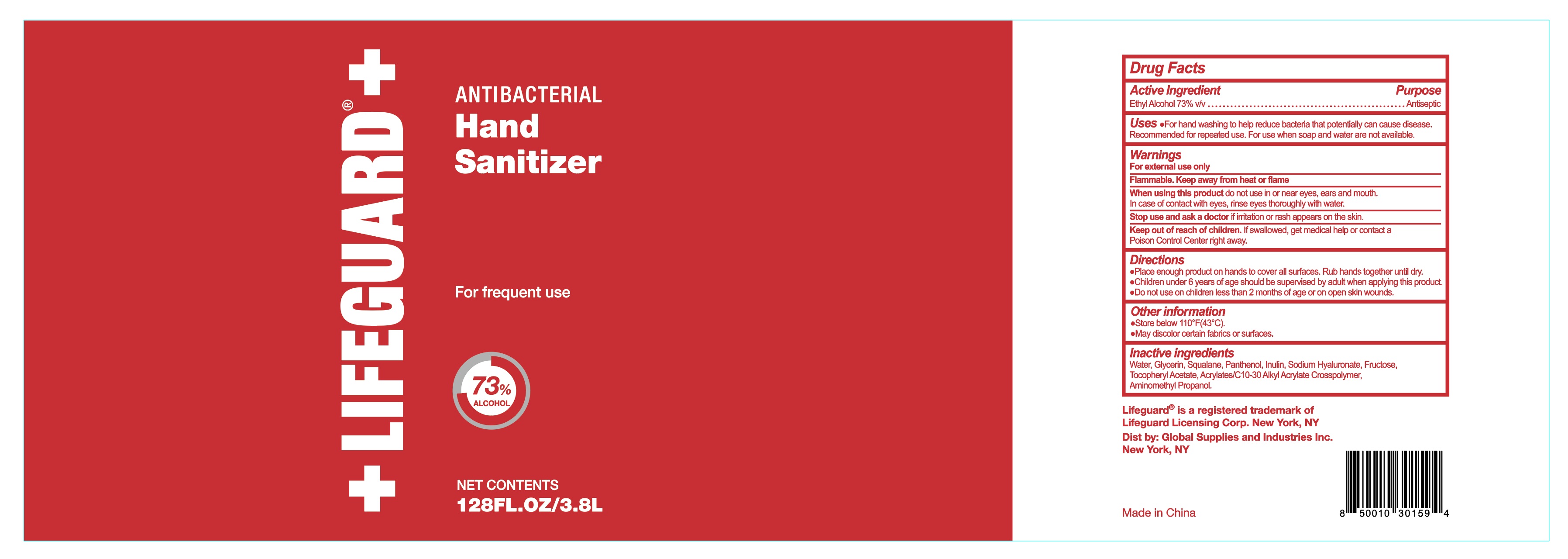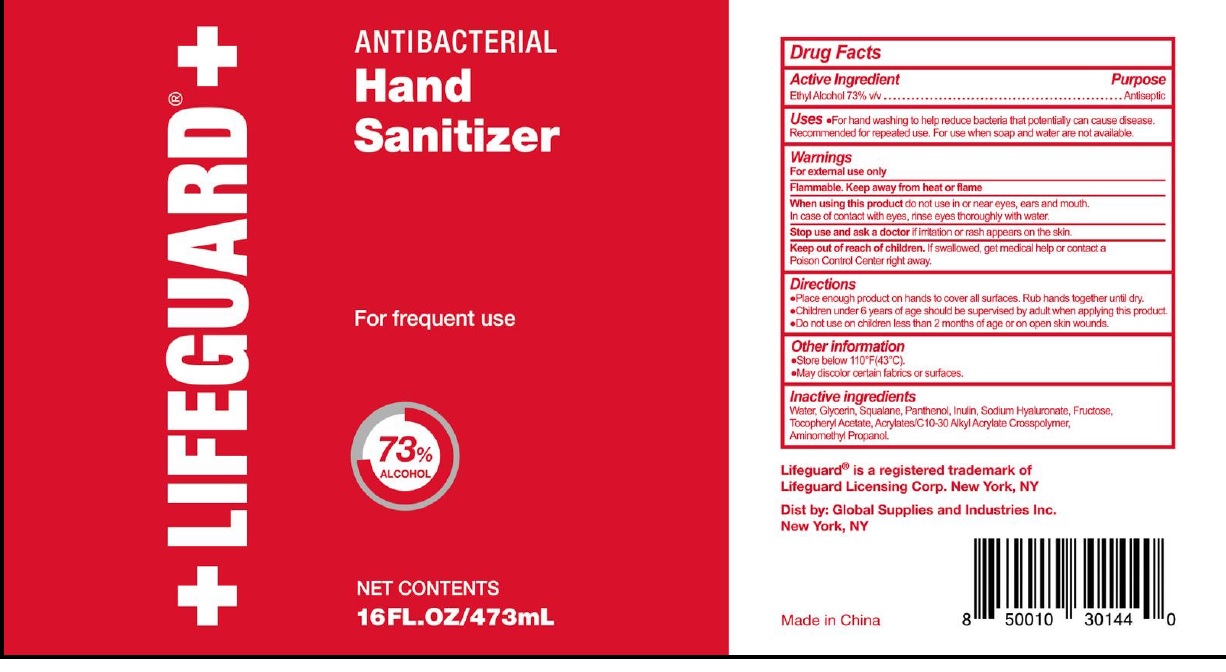 DRUG LABEL: Antibacterial Hand Sanitizer
NDC: 77879-002 | Form: LIQUID
Manufacturer: BT Supplies West Inc
Category: otc | Type: HUMAN OTC DRUG LABEL
Date: 20220209

ACTIVE INGREDIENTS: ALCOHOL 0.73 mL/1 mL
INACTIVE INGREDIENTS: WATER; GLYCERIN; SQUALANE; PANTHENOL; INULIN; HYALURONATE SODIUM; FRUCTOSE; .ALPHA.-TOCOPHEROL ACETATE; CARBOMER INTERPOLYMER TYPE A (ALLYL SUCROSE CROSSLINKED); AMINOMETHYLPROPANOL

Antibacterial Hand Sanitizer

Active ingredient

Ethyl Alcohol 73% v/v

Purpose

Antiseptic

Uses

- For hand washing to help reduce bacteria that potentially can cause disease. Recommended for repeated use. For use when soap and water are not available.

Warnings

For external use only.

Flammable. Keep away from fire or flame.

When using this product

do not use in or near eyes, ears and mouth. In case of contact with eyes, rinse eyes thoroughly with water.

Stop use and ask a doctor

if irritation or rash appears on the skin.

Keep out of reach of children.

If swallowed, get medical help or contact a Poison Control Center right away.

Directions

- Place enough product on hands to cover all surfaces. Rub hands together until dry.
- Children under 6 years of age should be supervised by adult when applying this product.
- Do not use on children less than 2 months of age or on open skin wounds.

Other information

- Store below 110°F (43°C).
- May discolor ertain fabrics or surfaces.

Inactive ingredients

Water, Glycerin, Squalane, Panthenol, Inulin, Sodium Hyaluronate, Fructose, Tocopheryl Acetate, Acrylates/C10-30Alkyl Acrylate Crosspolymer, Aminomethyl Propanol.